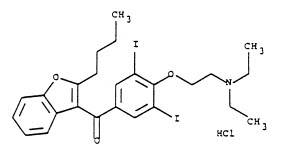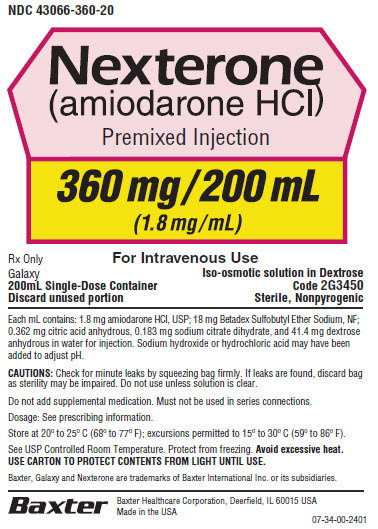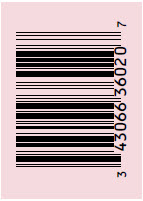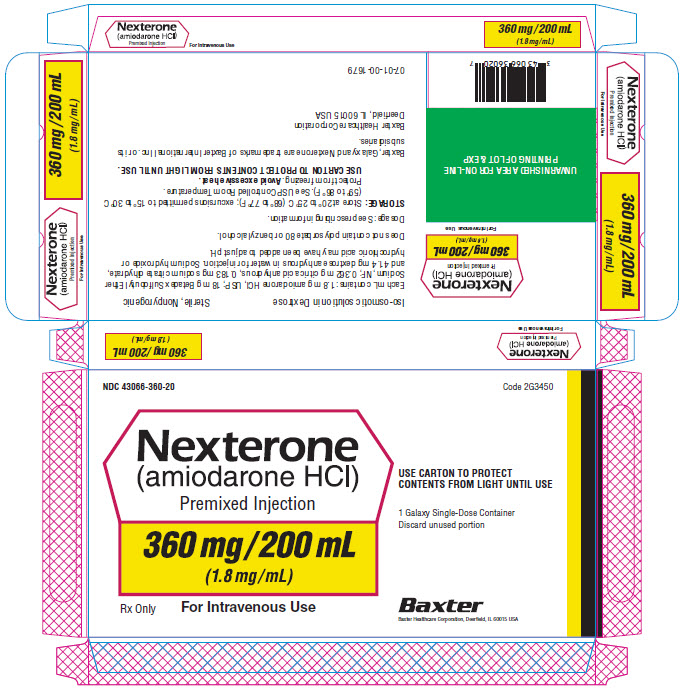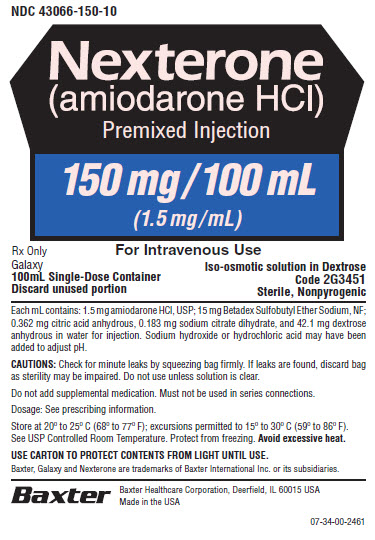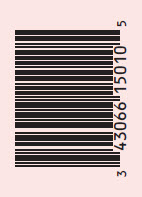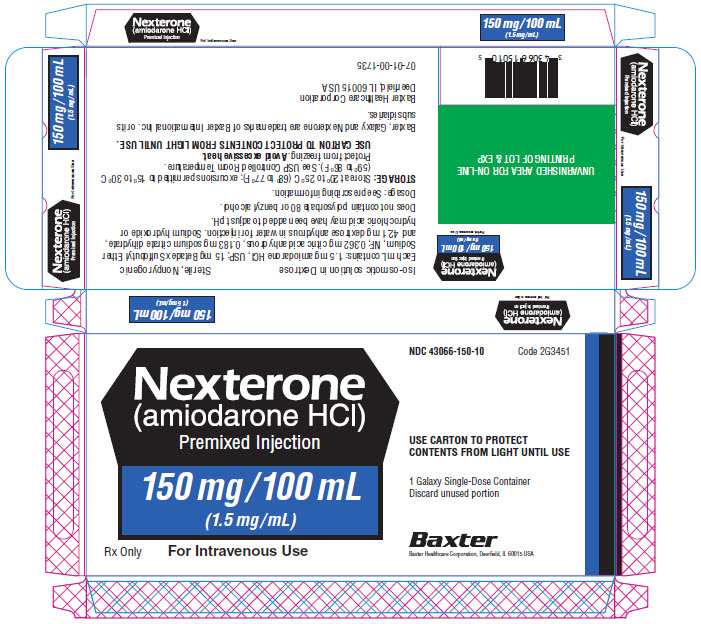 DRUG LABEL: Nexterone
NDC: 43066-150 | Form: INJECTION, SOLUTION
Manufacturer: Baxter Healthcare Company
Category: prescription | Type: HUMAN PRESCRIPTION DRUG LABEL
Date: 20250221

ACTIVE INGREDIENTS: AMIODARONE HYDROCHLORIDE 1.5 mg/1 mL
INACTIVE INGREDIENTS: BETADEX SULFOBUTYL ETHER SODIUM 15 mg/1 mL; ANHYDROUS CITRIC ACID 0.362 mg/1 mL; TRISODIUM CITRATE DIHYDRATE 0.183 mg/1 mL; ANHYDROUS DEXTROSE 42.1 mg/1 mL; SODIUM HYDROXIDE; HYDROCHLORIC ACID; WATER

HIGHLIGHTS OF PRESCRIBING INFORMATION

These highlights do not include all the information needed to use NEXTERONE safely and effectively. See full prescribing information for NEXTERONE.
NEXTERONE (amiodarone HCl) Premixed Injection for intravenous use
Initial U.S. Approval: 1985

RECENT MAJOR CHANGES

Warnings and Precautions, Primary Graft Dysfunction (PGD) (5.3) 02/2025

1 INDICATIONS AND USAGE

NEXTERONE Premixed Injection is an antiarrhythmic agent indicated for treatment and prophylaxis of ventricular fibrillation (VF) and hemodynamically unstable ventricular tachycardia (VT) in patients refractory to other therapy. (1)

2 DOSAGE AND ADMINISTRATION

1. The recommended starting dosing regimen is: (2)
  1. Initial Load: 150 mg in 100 mL infused over 10 minutes
  2. Followed by: 1 mg/min for 6 hours
  3. Followed by: 0.5 mg/min thereafter
2. For breakthrough episodes of VF or hemodynamically unstable VT, repeat the Initial Load (2)

3 DOSAGE FORMS AND STRENGTHS

Injection, 1.5 mg/mL (150 mg/100 mL) Premixed in Dextrose (3)

Injection, 1.8 mg/mL (360 mg/200 mL) Premixed in Dextrose (3)

4 CONTRAINDICATIONS

NEXTERONE Premixed Injection, is contraindicated in patients with (4):

1. Known hypersensitivity to any of the components of NEXTERONE Premixed Injection, including iodine
2. Cardiogenic shock
3. Marked sinus bradycardia
4. Second- or third-degree atrio-ventricular (AV) block unless a pacemaker is available.

5 WARNINGS AND PRECAUTIONS

1. Hypotension: Slow the infusion; as needed, add vasopressor drugs, positive inotropic agents, and volume expansion. (5.2)
2. Primary Graft Dysfunction (PGD) Post Cardiac Transplant (5.3)
3. Bradycardia and AV block: Slow the infusion or discontinue. (5.4)

6 ADVERSE REACTIONS

1. The most common adverse reactions (1-2%) leading to discontinuation of intravenous amiodarone therapy are hypotension, asystole/cardiac arrest/pulseless electrical activity, VT, and cardiogenic shock. (6)
2. Other important adverse reactions are torsade de pointes, congestive heart failure, and liver function test abnormalities. (6)

To report SUSPECTED ADVERSE REACTIONS, contact Baxter Healthcare at 1-866-888-2472 or FDA at 1-800-FDA-1088 or www.fda.gov/medwatch.

7 DRUG INTERACTIONS

1. Amiodarone is a substrate for CYP3A and CYP2C8, so inhibitors and inducers affect amiodarone exposure (7)
2. Amiodarone inhibits p-glycoprotein and CYP1A2, CYP2C9, CYP2D6, and CYP3A, increasing exposure to other drugs (7)

8 USE IN SPECIFIC POPULATIONS

1. Pregnancy: Use NEXTERONE Premixed Injection during pregnancy only if the potential benefit to the mother justifies the risk to the fetus (8.1).
2. Nursing mothers: Advise mothers to discontinue breast feeding (8.2).

FULL PRESCRIBING INFORMATION

1 INDICATIONS AND USAGE

NEXTERONE Premixed Injection is indicated for initiation of treatment and prophylaxis of frequently recurring ventricular fibrillation (VF) and hemodynamically unstable ventricular tachycardia (VT) in patients refractory to other therapy.

2 DOSAGE AND ADMINISTRATION

2.1 General Considerations

Inspect parenteral drug products for particulate matter and discoloration prior to administration, whenever solution and container permit, solution should be clear. Visually inspect the container. If the administration port protector is damaged, detached or not present, discard the container as the solution path sterility may be compromised. Check for minute leaks prior to use by squeezing the bag firmly. If leaks are detected, discard solution as sterility may be impaired. Protect from light until ready to use.

NEXTERONE Premixed Injection is available in GALAXY containers as a single-use, ready-to-use, iso-osmotic solution in dextrose for intravenous administration. No further dilution is required. Discard any unused portion after use.

Administer NEXTERONE Premixed Injection, whenever possible, through a central venous catheter dedicated to that purpose. Use an in-line filter during administration.

2.2 Recommended Dosage

NEXTERONE Premixed Injection response can vary. Monitor patient response and adjust dose accordingly. In controlled clinical trials, mean daily doses above 2100 mg were associated with an increased risk of hypotension.

Table 1: NEXTERONE Premixed Injection Dosage Recommendations
Loading Infusion | First Rapid | 150 mg over the FIRST 10 minutes (15 mg/min). Directly infuse NEXTERONE Premixed Injection (150 mg/100 mL; 1.5 mg/mL) at a rate of 10 mL/min.
 | Followed by Slow | 360 mg over the NEXT 6 hours (1 mg/min). Directly infuse NEXTERONE Premixed Injection (360 mg/200 mL; 1.8 mg/mL) at a rate of 0.556 mL/min. 540 mg over the REMAINING 18 hours (0.5 mg/min) Decrease the rate to 0.278 mL/min.
Maintenance Infusion |  | After the first 24 hours, continue the maintenance infusion 720 mg per 24 hour period (0.5 mg/min) Directly infuse NEXTERONE Premixed Injection (360 mg/200 mL; 1.8 mg/mL) at a rate of 0.278 mL/min).
Breakthrough VF or Hemodynamically Unstable VT |  | 150 mg supplemental infusion over 10 minutes (15 mg/min). Directly infuse NEXTERONE Premixed Injection (150 mg/100mL; 1.5 mg/mL) at a rate of 10 mL/min.

Admixture Incompatibility
Amiodarone in D5W Injection forms precipitates with the drugs shown in Table 2. If co-administration of the following drugs is necessary, use separate intravenous administration lines.

Table 2: Y-SITE INJECTION INCOMPATIBILITY
Drug | Vehicle | Amiodarone Concentration
Aminophylline | D5W; NS | 4 mg/mL
Amoxicillin Sodium-Clavulanic Acid | unknown | 12.5 mg/mL
Ampicillin Sodium-Sulbactam Sodium | NS | 6 mg/mL
Argatroban | D5W | 1.8 mg/mL
Bivalirudin | D5W | 4 mg/mL
Cefamandole Nafate | D5W | 4 mg/mL
Cefazolin Sodium | D5W | 4 mg/mL
Ceftazidime | D5W | 6 mg/mL
Digoxin | D5W | 6 mg/mL
Furosemide (10 mg/mL) | D5W | 6 mg/mL
Mezlocillin Sodium | D5W | 4 mg/mL
Heparin Sodium | D5W | --
Imipenem-Cilastin Sodium | D5W | 6 mg/mL
Magnesium Sulfate (500 mg/mL) | D5W | 6 mg/mL
Micafungin | NS | 4 mg/mL
Piperacillin Sodium –Tazobactam Sodium | D5W | 6 mg/mL
Potassium Phosphates | D5W | 6 mg/mL
Sodium Bicarbonate | D5W | 3 mg/mL
Sodium Nitroprusside | D5W | 1.5, 6 and 15 mg/mL
Sodium Phosphates | D5W | 6 mg/mL
D5W = Dextrose 5% in Sterile Water, NS = Normal Saline

2.3 Transition From Intravenous Amiodarone to Oral Amiodarone

Table 3 provides suggested doses of oral amiodarone to be initiated after varying durations of NEXTERONE infusion.

Table 3: RECOMMENDATIONS FOR ORAL DOSAGE AFTER INTRAVENOUS INFUSION
Duration of Amiodarone Infusion [Assuming a 720 mg/day infusion (0.5 mg/min).] | Initial Daily Dose of Oral Amiodarone
Less than 1 week | 800 to 1600 mg
1 to 3 weeks | 600 to 800 mg
More than 3 weeks [Intravenous amiodarone is not intended for maintenance treatment.] | 400 mg

3 DOSAGE FORMS AND STRENGTHS

Injection, 1.5 mg/mL (150 mg/100 mL) Premixed in Dextrose

Injection, 1.8 mg/mL (360 mg/200 mL) Premixed in Dextrose

4 CONTRAINDICATIONS

NEXTERONE Premixed Injection is contraindicated in patients with:

1. Known hypersensitivity to any of the components of NEXTERONE Premixed Injection, including iodine [see Warnings and Precautions (5.9)].
2. Cardiogenic shock.
3. Marked sinus bradycardia.
4. Second- or third-degree atrioventricular (AV) block unless a functioning pacemaker is available.

5 WARNINGS AND PRECAUTIONS

5.1 Persistence of Adverse Effects

Because of the long half-life of amiodarone (9 to 36 days) and its metabolite desethylamiodarone (9 to 30 days), adverse reactions or interactions, as well as observed adverse effects, can persist following amiodarone withdrawal.

5.2 Hypotension

Hypotension, the most common adverse reaction seen with intravenous amiodarone seen most often in the first several hours of treatment and is likely related to the rate of infusion. In some cases, hypotension may be refractory and result in a fatal outcome. Hypotension necessitating alterations in intravenous amiodarone therapy was reported in 3% of patients, with permanent discontinuation required in less than 2% of patients.

Treat hypotension initially by slowing the infusion; additional standard therapy may be needed, including the following: vasopressor drugs, positive inotropic agents, and volume expansion. Monitor the initial rate of infusion closely and do not exceed the recommended rate [see Dosage and Administration (2)].

5.3 Primary Graft Dysfunction (PGD) Post Cardiac Transplant

In retrospective studies, amiodarone use in transplant recipients prior to heart transplants has been associated with an increased risk of PGD. PGD is a life-threatening complication of heart transplantation that presents as a left, right or biventricular dysfunction occurring within the first 24 hours of transplant surgery for which there is no identifiable secondary cause (see section 6.2). Severe PGD may be irreversible. For patients who are on the heart transplant waiting list, consideration should be given to use an alternative antiarrhythmic drug as early as possible before transplant.

5.4 Bradycardia and Atrioventricular Block

NEXTERONE Premixed Injection causes bradycardia and AV block which may require slowing the infusion rate or discontinuing NEXTERONE. In some patients, inserting a pacemaker is required. Have a temporary pacemaker available when treating a patient predisposed to bradycardia or AV block.

5.5 Hepatic Injury

Acute hepatocellular necrosis leading to hepatic coma, acute renal failure, and death has been associated with the administration of intravenous amiodarone. Intravenous infusions at much higher concentrations and rates of infusion than those recommended appear to increase this risk [see Dosage and Administration (2)].

Carefully monitor patients receiving NEXTERONE Premixed Injection for evidence of progressive hepatic injury. Consider reducing the rate of administration or withdrawing NEXTERONE Premixed Injection if hepatic injury occurs.

5.6 Proarrhythmia

NEXTERONE Premixed Injection may cause a worsening of existing arrhythmias or precipitate a new arrhythmia, sometimes leading to fatal outcomes [see Adverse Reactions (6.2)]. Proarrhythmia, primarily torsade de pointes (TdP), has been associated with prolongation, by intravenous amiodarone. Although QTc prolongation occurred frequently in patients receiving intravenous amiodarone, TdP or new-onset VF occurred infrequently (less than 2%). Monitor patients for QTc prolongation during infusion with NEXTERONE Premixed Injection. Reserve the combination of amiodarone with other antiarrhythmic therapies that prolong the QTc to patients with life-threatening ventricular arrhythmias who are incompletely responsive to a single agent.

Correct hypokalemia, hypomagnesemia or hypocalcemia whenever possible before initiating treatment with NEXTERONE Premixed Injection, as these disorders can exaggerate the degree of QTc prolongation and increase the potential for TdP. Give special attention to electrolyte and acid-base balance in patients experiencing severe or prolonged diarrhea or in patients receiving concomitant diuretics and laxatives.

5.7 Pulmonary Injury

Early-onset Pulmonary Toxicity
There have been postmarketing reports of acute-onset (days to weeks) pulmonary injury in patients treated with intravenous amiodarone. Findings have included pulmonary infiltrates and masses on X-ray, pulmonary fibrosis, bronchospasm, wheezing, fever, dyspnea, cough, hemoptysis, and hypoxia. Two percent (2%) of patients were reported to have adult respiratory distress syndrome (ARDS) during clinical studies involving 48 hours of therapy.

Some cases have progressed to respiratory failure or death. Monitor for new respiratory symptoms and evaluate appropriately. Obtain a baseline chest X-ray and pulmonary function tests in patients who are expected to be receiving amiodarone chronically.

5.8 Loss of Vision

Cases of optic neuropathy and optic neuritis, usually resulting in visual impairment, have been reported in patients treated with oral amiodarone or intravenous amiodarone. In some cases, visual impairment has progressed to permanent blindness. Optic neuropathy and neuritis may occur at any time following initiation of therapy. Perform an ophthalmic examination if symptoms of visual impairment appear, such as changes in visual acuity and decreases in peripheral vision. Re-evaluate the necessity of amiodarone therapy if optic neuropathy or neuritis is suspected.

5.9 Thyroid Abnormalities

NEXTERONE Premixed Injection inhibits peripheral conversion of throxine (T4) to triiodothyronine (T3) and may cause increased T3 levels, and increased levels of inactive reverse T3 (rT3) in clinically euthyroid patients. Monitor thyroid function prior to treatment and periodically thereafter, particularly in elderly patients, and in any patient with a history of thyroid nodules, goiter, or other thyroid dysfunction.

Hyperthyroidism may induce arrhythmia breakthrough. If any new signs of arrhythmia appear, the possibility of hyperthyroidism should be considered.

Antithyroid drugs, β-adrenergic blockers, temporary corticosteroid therapy may be necessary to treat the symptoms of hyperthyroidism. The action of antithyroid drugs may be delayed in amiodarone-induced thyrotoxicosis because of substantial quantities of preformed thyroid hormones stored in the gland. Radioactive iodine therapy is contraindicated because of the low radioiodine uptake associated with amiodarone-induced hyperthyroidism.

NEXTERONE Premixed Injection induced hyperthyroidism may be followed by a transient period of hypothyroidism. In some clinically hypothyroid amiodarone-treated patients, free thyroxine index values may be normal. Manage hypothyroidism by reducing the dose of or discontinuing amiodarone and thyroid hormone supplementation.

5.10 Neonatal Injury

Amiodarone can cause fetal harm when administered to a pregnant woman. Fetal exposure may increase the potential for adverse experiences including cardiac, thyroid, neurodevelopmental, neurological and growth effects in neonate. Inform the patient of the potential hazard to the fetus if NEXTERONE Premixed Injection is administered during pregnancy or if the patient becomes pregnant while taking NEXTERONE [see Pregnancy (8.1)].

5.11 Hypersensitivity Reactions

Anaphylactic/anaphylactoid reactions have been reported with intravenous amiodarone including shock (sometimes fatal), cardiac arrest, and the following manifestations: hypotension, tachycardia, hypoxia, cyanosis, rash, Stevens-Johnson syndrome, flushing, hyperhidrosis and cold sweat.

5.12 Phlebitis

Infusion site phlebitis has occurred in patients receiving intravenous amiodarone. Intravenous amiodarone concentrations greater than 3 mg/mL have been associated with a high incidence of peripheral vein phlebitis.

6 ADVERSE REACTIONS

The following adverse reactions are described elsewhere in labeling:

- Hypotension [see Warnings and Precautions (5.2)]
- Primary Graft Dysfunction (PGD) Post Cardiac Transplant [see Warnings and Precautions (5.3)]
- Hepatic injury [see Warnings and Precautions (5.5)]
- Proarrhythmia [see Warnings and Precautions (5.6)]
- Pulmonary injury [see Warnings and Precautions (5.7)]
- Thyroid injury [see Warnings and Precautions (5.9)]
- Hypersensitivity [see Warnings and Precautions (5.11)]

6.1 Clinical Trials Experience

Because clinical trials are conducted under widely varying conditions, adverse reaction rates observed in the clinical trials of a drug cannot be directly compared to rates in the clinical trials of another drug and may not reflect the rates observed in practice.

In a total of 1836 patients in controlled and uncontrolled clinical trials, 14% of patients received intravenous amiodarone for at least one week, 5% received it for at least 2 weeks, 2% received it for at least 3 weeks, and 1% received it for more than 3 weeks. The mean duration of therapy in these studies was 5.6 days; median exposure was 3.7 days.

The most important adverse reactions were hypotension, asystole/cardiac arrest/pulseless electrical activity (PEA), cardiogenic shock, congestive heart failure, bradycardia, liver function test abnormalities, VT, and AV block.

Overall, treatment was discontinued for about 9% of the patients because of adverse reactions. The most common adverse reactions leading to discontinuation of intravenous amiodarone therapy were hypotension (1.6%), asystole/cardiac arrest/PEA (1.2%), VT (1.1%), and cardiogenic shock (1%).

Other adverse reactions reported in less than 2% of patients receiving intravenous amiodarone in controlled and uncontrolled studies included the following: abnormal kidney function, diarrhea, shock, sinus bradycardia, Stevens-Johnson syndrome, VF, and vomiting.

6.2 Post-Marketing Experience

The following adverse reactions have been reported in the post-marketing experience during or in close temporal relationship to intravenous amiodarone administration. Because these reactions are reported voluntarily from a population of uncertain size, it is not always possible to reliably estimate their frequency or establish a causal relationship to drug exposure.

Blood and Lymphatic System Disorders: pancytopenia, neutropenia, hemolytic anemia, aplastic anemia, thrombocytopenia, and granulocytosis.

Cardiac Disorders: sinus node dysfunction (sinus arrest, sinoatrial block), intraventricular conduction disorders including bundle branch block and infra-HIS block, bradycardia (sometimes fatal), ventricular extrasystoles, and antegrade conduction via an accessory pathway.

Endocrine Disorders: syndrome of inappropriate antidiuretic hormone secretion (SIADH).

Eye Disorders: visual field defect and blurred vision.

Gastrointestinal Disorders: pancreatitis.

General Disorders and Administration Site Conditions: infusion site reactions, including thombosis, phlebitis, thrombophlebitis, cellulitis, pain, induration, edema, inflammation, urticaria, pruritus, erythema, pigment changes, hypoesthesia, skin sloughing, extravasation possibly leading to venous/infusion site necrosis, and granuloma.

Hepatobiliary Disorders: cholestasis, cirrhosis, jaundice, alkaline phosphatase and blood lactate dehydrogenase increase.

Injury, poisoning and procedural complications: transplant dysfunction (primary graft dysfunction post cardiac transplant).

Musculoskeletal and Connective Tissue Disorders: myopathy, muscle weakness, rhabdomyolysis, muscle spasms, and back pain.

Neoplasms benign, malignant and unspecified (incl cysts and polyps) Disorders: thyroid nodules/thyroid cancer.

Nervous System Disorders: intracranial pressure increased, pseudotumor cerebri, tremor, dizziness and hypoesthesia.

Psychiatric Disorders: confusional state, hallucination, disorientation, and delirium.

Renal and Urinary Disorders: acute renal failure (sometimes fatal), renal impairment, renal insufficiency, and blood creatinine increased.

Reproductive Disorders and Breast Disorders: Epididymitis

Respiratory, Thoracic and Mediastinal Disorders: interstitial pneumonitis, bronchiolitis obliterans organizing pneumonia (possibly fatal), pulmonary alveolar hemorrhage, pulmonary phospholipidoisis, pleural effusion, bronchospasm, dyspnea, cough, hemoptysis, wheezing, and hypoxia.

Skin and Subcutaneous Tissue Disorders: toxic epidermal necrolysis (sometimes fatal), Stevens-Johnson syndrome, exfoliative dermatitis, erythema multiforme, skin cancer, pruritus, angioedema, and urticaria.

Vascular Disorders: vasculitis and flushing.

7 DRUG INTERACTIONS

Drug interactions with amiodarone are described in Table 4 below.

Table 4: Amiodarone Drug Interactions
Concomitant Drug Class/Name | Examples | Clinical Comment
QT Prolonging Drugs | class I and III antiarrhythmics, lithium, certain phenothiazines, tricyclic antidepressants, certain fluoroquinolone and macrolide antibiotics, azole antifungals, halogenated inhalation anesthetic agents | Increased risk of Torsade de Pointes. Avoid concomitant use.
Negative Chronotropes | digoxin, beta blockers, verapamil, diltiazem, clonidine, ivabradine | Potentiates the electrophysiologic and hemodynamic effects of amiodarone, resulting in bradycardia, sinus arrest and AV block. Monitor heart rate.
CYP450 Inhibitors | Grapefruit juice, certain fluoroquinolone and macrolide antibiotics, azole antifungals, cimetidine | Increased exposure of amiodarone. Avoid concomitant use.
CYP450 Inducers | St. John’s Wort | Reduced amiodarone serum levels
Cyclosporine |  | Increased plasma levels of cyclosporine have been reported resulting in elevated creatinine, despite reduction of cyclosporine dose. Monitor cyclosporine drug levels and renal function with concomitant use.
Cholestyramine |  | Reduced amiodarone serum levels
Antiarrhythmics | quinidine, procainamide, flecainide | Reserve concomitant use for patients who are unresponsive to a single agent. Antiarrhythmic metabolism inhibited by amiodarone. Initiate antiarrhythmic at a lower than usual dose and monitor patient carefully. Reduce dose levels of previously administered antiarrhythmic by 30 to 50% for several days after transitioning to oral amiodarone. Evaluate continued need for antiarrhythmic.
Digoxin |  | Increased digoxin concentration. Reduce digoxin by half or discontinue. If continued, monitor for evidence of toxicity.
HMG-CoA Reductase Inhibitors | simvastatin, lovastatin, atorvastatin | Increased plasma concentration of HMG-CoA reductase inhibitor. Limit the dose of lovastatin to 40 mg. Limit the coadministered dose of simvastatin to 20 mg. Lower starting dose of other CYP3A4 substrates may be required.
Warfarin |  | Potentiates anticoagulant response and can result in serious or fatal bleeding. Coadministration increases INR by 100% after 3 to 4 days. Reduce warfarin dose by one-third to one-half and monitor INR.
Phenytoin |  | Increased steady state levels of phenytoin. Monitor phenytoin levels.
Hepatitis C direct acting antiviral | Sofosbuvir | Cases of symptomatic bradyarrhythmia requiring pacemaker insertion have been reported in patients on oral maintenance amiodarone who initiated therapy with Sofosbuvir.

8 USE IN SPECIFIC POPULATIONS

8.1 Pregnancy

Risk Summary
Available data from postmarketing reports and published case series indicate that amiodarone use in pregnant women may increase the risk for fetal adverse effects including neonatal hypo- and hyperthyroidism, neonatal bradycardia, neurodevelopmental abnormalities, preterm birth and fetal growth restriction. Amiodarone and its metabolite, desethylamiodarone (DEA), cross the placenta. Untreated underlying arrhythmias, including ventricular arrhythmias, during pregnancy pose a risk to the mother and fetus (see Clinical Considerations). In animal studies, administration of amiodarone to rabbits, rats, and mice during organogenesis resulted in embryo-fetal toxicity at doses less than the maximum recommended human maintenance dose (see Data). Advise pregnant women of the potential risk to a fetus.

The estimated background risk of major birth defects and miscarriage for the indicated population is unknown. All pregnancies have a background risk of birth defect, loss or other adverse outcomes. In the U.S. general population, the estimated background risk of major birth defects and miscarriage in clinically recognized pregnancies is 2%-4% and 15%‑20%, respectively.

Clinical Considerations
Disease-associated maternal and or embryo/fetal Risk
The incidence of ventricular tachycardia is increased and may be more symptomatic during pregnancy. Ventricular arrhythmias most often occur in pregnant women with underlying cardiomyopathy, congenital heart disease, valvular heart disease, or mitral valve prolapse. Most tachycardia episodes are initiated by ectopic beats and the occurrence of arrhythmia episodes may therefore, increase during pregnancy due to the increased propensity to ectopic activity. Breakthrough arrhythmias may also occur during pregnancy, as therapeutic treatment levels may be difficult to maintain due to the increased volume of distribution and increased drug metabolism inherent in the pregnant state.

Fetal/Neonatal adverse reactions
Amiodarone and its metabolite have been shown to cross the placenta. Adverse fetal effects associated with maternal amiodarone use during pregnancy may include neonatal bradycardia, QT prolongation, and periodic ventricular extrasystoles, neonatal hypothyroidism (with or without goiter) detected antenatally or in the newborn and reported even after a few days of exposure, neonatal hyperthyroxinemia, neurodevelopmental abnormalities independent of thyroid function, including speech delay and difficulties with written language and arithmetic, delayed motor development, and ataxia, jerk nystagmus with synchronous head titubation, fetal growth restriction, and premature birth. Monitor the newborn for signs and symptoms of thyroid disorder and cardiac arrhythmias.

Labor and Delivery
Risk of arrhythmias may increase during labor and delivery.

Data
Animal Data
In pregnant rats and rabbits during the period of organogenesis, an amiodarone HCl dose of 25 mg/kg/day (approximately 0.4 and 0.9 times, respectively, the maximum recommended human maintenance dose*) had no adverse effects on the fetus. In the rabbit, 75 mg/kg/day (approximately 2.7 times the maximum recommended human maintenance dose*) caused abortions in greater than 90% of the animals. In the rat, doses of 50 mg/kg/day or more were associated with slight displacement of the testes and an increased incidence of incomplete ossification of some skull and digital bones; at 100 mg/kg/day or more, fetal body weights were reduced; at 200 mg/kg/day, there was an increased incidence of fetal resorption (approximately 0.8, 1.6 and 3.2 times the maximum recommended human maintenance dose*). Adverse effects on fetal growth and survival also were noted in one of two strains of mice at a dose of 5 mg/kg/day (approximately 0.04 times the maximum recommended human maintenance dose*).

*600 mg in a 60 kg patient (doses compared on a body surface area basis)

8.2 Lactation

Risk Summary
Amiodarone and one of its major metabolites, DEA, are present in breastmilk at between 3.5% and 45% of the maternal weight-adjusted dosage of amiodarone. There are cases of hypothyroidism and bradycardia in breastfed infants, although it is unclear if these effects are due to amiodarone exposure in breastmilk. Breastfeeding is not recommended during treatment with NEXTERONE Premixed Injection [see Warnings and Precautions (5.9)].

8.3 Females and Males of Reproductive Potential

Infertility
Based on animal fertility studies, NEXTERONE Premixed Injection may reduce female and male fertility. It is not known if this effect is reversible. [see Nonclinical Toxicology (13.1)].

8.4 Pediatric Use

The safety and effectiveness of amiodarone in pediatric patients have not been established. In a pediatric trial of 61 patients, aged 30 days to 15 years, hypotension (36%), bradycardia (20%), and AV block (15%) were common dose-related adverse reactions and were severe or life-threatening in some cases. Injection site reactions were seen in 5 (25%) of the 20 patients receiving intravenous amiodarone through a peripheral vein irrespective of dose regimen.

8.5 Geriatric Use

Clinical studies of amiodarone did not include sufficient numbers of subjects aged 65 and over to determine whether they respond differently from younger subjects. Other reported clinical experience has not identified differences in responses between the elderly and younger patients. Carefully consider dose selection in an elderly patient. In general, start at the low end of the dosing range in the elderly to reflect the greater frequency of decreased hepatic, renal, or cardiac function, and concomitant disease or other drug therapy.

10 OVERDOSAGE

There have been cases, some fatal, of amiodarone overdose. Effects of an inadvertent overdose of intravenous amiodarone include hypotension, cardiogenic shock, bradycardia, AV block, and hepatotoxicity. Treat hypotension and cardiogenic shock by slowing the infusion rate or with standard therapy: vasopressor drugs, positive inotropic agents, and volume expansion. Bradycardia and AV block may require temporary pacing. Monitor hepatic enzyme concentrations closely. Neither amiodarone nor DEA is dialyzable.

11 DESCRIPTION

NEXTERONE Premixed Injection contains amiodarone HCl (C25H29I2NO3•HCl), a class III antiarrhythmic drug. Amiodarone HCl is
(2-butyl-3-benzo-furanyl)[4-[2-(diethylamino)ethoxy]-3,5-diiodophenyl]methanone hydrochloride.

Amiodarone HCl has the following structural formula:

Amiodarone HCl is a white to slightly yellow crystalline powder and is very slightly soluble in water. It has a molecular weight of 681.78 and contains 37.3% iodine by weight. NEXTERONE Premixed Injection is a sterile clear, colorless to slightly yellow solution visually free from particulates. NEXTERONE Premixed Injection is available as a ready-to-use, nonpyrogenic, iso-osmotic solution for intravenous administration in 100-mL GALAXY containers with 150 mg of amiodarone HCl, USP (1.5 mg/mL) in dextrose, and 200-mL GALAXY containers with 360 mg of amiodarone HCl, USP (1.8 mg/mL) in dextrose.

NEXTERONE Premixed Injection (150 mg/100 mL, 1.5 mg/mL):

Each mL contains 1.5 mg of amiodarone HCl, USP, 15 mg Betadex Sulfobutyl Ether Sodium, NF, 0.362 mg citric acid anhydrous, 0.183 mg sodium citrate dihydrate and 42.1 mg dextrose anhydrous in water for injection. Sodium hydroxide or hydrochloric acid may have been added to adjust pH.

NEXTERONE Premixed Injection (360 mg/200 mL, 1.8 mg/mL):

Each mL contains 1.8 mg of amiodarone HCl, USP, 18 mg Betadex Sulfobutyl Ether Sodium, NF, 0.362 mg citric acid anhydrous, 0.183 mg sodium citrate dihydrate and 41.4 mg dextrose anhydrous in water for injection. Sodium hydroxide or hydrochloric acid may have been added to adjust pH.

NEXTERONE Premixed Injection does not contain polysorbate 80 or benzyl alcohol.

The GALAXY container is fabricated from a specially designed multilayered plastic. Solutions are in contact with the polyethylene layer of the container and can leach out certain chemical components of the plastic in very small amounts within the expiration period. The suitability and safety of the plastic have been confirmed in tests in animals according to the USP biological tests for plastic containers, as well as by tissue culture toxicity studies.

12 CLINICAL PHARMACOLOGY

12.1 Mechanism of Action

Amiodarone is considered a class III antiarrhythmic drug, but it possesses electrophysiologic characteristics of all four Vaughan Williams classes. Like class I drugs, amiodarone blocks sodium channels at rapid pacing frequencies, and like class II drugs, amiodarone exerts a noncompetitive antisympathetic action. One of its main effects, with prolonged administration, is to lengthen the cardiac action potential, a class III effect. The negative chronotropic effect of amiodarone in nodal tissues is similar to the effect of class IV drugs. In addition to blocking sodium channels, amiodarone blocks myocardial potassium channels, which contributes to slowing of conduction and prolongation of refractoriness. The antisympathetic action and the block of calcium and potassium channels are responsible for the negative dromotropic effects on the sinus node and for the slowing of conduction and prolongation of refractoriness in the atrioventricular (AV) node. Its vasodilatory action can decrease cardiac workload and consequently myocardial oxygen consumption.

Intravenous amiodarone administration prolongs intranodal conduction (Atrial-His, AH) and refractoriness of the atrioventricular node (ERP AVN) but has little or no effect on sinus cycle length (SCL), refractoriness of the right atrium and right ventricle (ERP RA and ERP RV), repolarization (QTc), intraventricular conduction (QRS), and infra-nodal conduction (His-ventricular, HV). A comparison of the electrophysiologic effects of intravenous amiodarone and oral amiodarone is shown in the table below.

Table 5: EFFECTS OF INTRAVENOUS AND ORAL AMIODARONE ON ELECTROPHYSIOLOGIC PARAMETERS
Formulation | SCL | QRS | QTc | AH | HV | ERP RA | ERP RV | ERP AVN
Intravenous | ↔ | ↔ | ↔ | ↑ | ↔ | ↔ | ↔ | ↑
Oral | ↑ | ↔ | ↑ | ↑ | ↔ | ↑ | ↑ | ↑
↔No change

At higher doses (>10 mg/kg) of intravenous amiodarone, prolongation of the ERP RV and modest prolongation of the QRS have been seen. These differences between oral and IV administration suggest that the initial acute effects of intravenous amiodarone may be predominately focused on the AV node, causing an intranodal conduction delay and increased nodal refractoriness due to slow channel blockade (class IV activity) and noncompetitive adrenergic antagonism (class II activity).

12.2 Pharmacodynamics

Intravenous amiodarone has been reported to produce negative inotropic and vasodilatory effects in animals and humans. In clinical studies of patients with refractory VF or hemodynamically unstable VT, treatment-emergent, drug-related hypotension occurred in 288 of 1836 patients (16%) treated with intravenous amiodarone. No correlations were seen between the baseline ejection fraction and the occurrence of clinically significant hypotension during infusion of intravenous amiodarone.

No data are available on the activity of DEA in humans, but in animals, it has significant electrophysiologic and antiarrhythmic effects generally similar to amiodarone itself. DEA's precise role and contribution to the antiarrhythmic activity of oral amiodarone are not certain. The development of maximal ventricular class III effects after oral amiodarone administration in humans correlates more closely with DEA accumulation over time than with amiodarone accumulation. On the other hand, after intravenous amiodarone administration, there is evidence of activity well before significant concentrations of DEA are attained [see Clinical Trials (14)].

There is no established relationship between drug concentration and therapeutic response for short-term intravenous use.

12.3 Pharmacokinetics

Absorption:
Amiodarone exhibits complex disposition characteristics after intravenous administration. Peak serum concentrations after single 5 mg/kg 15-minute intravenous infusions in healthy subjects range between 5 and 41 mg/L. Peak concentrations after 10-minute infusions of 150 mg intravenous amiodarone in patients with ventricular fibrillation (VF) or hemodynamically unstable ventricular tachycardia (VT) range between 7 and 26 mg/L. Because of rapid distribution, serum concentrations decline to 10% of peak values within 30 to 45 minutes after the end of the infusion. In clinical trials, after 48 hours of continued infusions (125, 500 or 1000 mg/day) plus supplemental (150 mg) infusions (for recurrent arrhythmias), amiodarone mean serum concentrations between 0.7 to 1.4 mg/L were observed (n=260).

Distribution:
From in vitro studies, the protein binding of amiodarone is >96%. Amiodarone and DEA cross the placenta and both appear in breast milk. Neither amiodarone nor DEA is dialyzable.

Elimination:
Amiodarone is eliminated primarily by hepatic metabolism and biliary excretion and there is negligible excretion of amiodarone or DEA in urine. In studies in healthy subjects following single intravenous administration (5 mg/kg of amiodarone over 15 min), the plasma concentration vs. time profile could be characterized by linear sum of four exponential terms with terminal elimination half-lives (t½) of 9 - 36 days for amiodarone and 9 - 30 days for DEA. The clearance of amiodarone and DEA ranged between 63 - 231 mL/h/kg and 140 - 400 ml/h/kg, respectively. In clinical studies of 2 to 7 days, clearance of amiodarone after intravenous administration in patients with VT and VF ranged between 220 and 440 mL/h/kg.

Metabolism:
N-desethylamiodarone (DEA) is the major active metabolite of amiodarone in humans. DEA serum concentrations above 0.05 mg/L are not usually seen until after several days of continuous infusion but with prolonged therapy reach approximately the same concentration as amiodarone. Amiodarone is metabolized to DEA by the cytochrome P450 (CYP450) enzyme group, specifically cytochrome P4503A (CYP3A) and CYP2C8. The CYP3A isoenzyme is present in both the liver and intestines.

Specific Populations:
Age: The pharmacokinetics of amiodarone and DEA are affected by age. Normal subjects over 65 years of age show lower clearances (about 100 mL/h/kg) than younger subjects (about 150 mL/h/kg) and an increase in t½ from about 20 to 47 days.

Sex: Pharmacokinetics of amiodarone and DEA are similar in males and females.

Renal Impairment:
Renal disease does not influence the pharmacokinetics of amiodarone or DEA.

Hepatic Impairment:
After a single dose of intravenous amiodarone to cirrhotic patients, significantly lower Cmax and average concentration values are seen for DEA, but mean amiodarone levels are unchanged.

Cardiac Disease:
In patients with severe left ventricular dysfunction, the pharmacokinetics of amiodarone are not significantly altered but the terminal elimination t½ of DEA is prolonged.

Although no dosage adjustment for patients with renal, hepatic, or cardiac abnormalities has been defined during chronic treatment with oral amiodarone, close clinical monitoring is prudent for elderly patients and those with severe left ventricular dysfunction.

Drug Interactions:

Effect of other drugs on amiodarone:
Cimetidine inhibits CYP3A and can increase serum amiodarone levels.

Grapefruit juice given to healthy volunteers increased amiodarone AUC
by 50% and Cmax by 84%, resulting in increased plasma levels of amiodarone.

Cholestyramine reduces enterohepatic circulation of amiodarone thereby increasing its elimination. This results in reduced amiodarone serum levels and half-life.

Effect of amiodarone on other drugs:
Amiodarone taken concomitantly with quinidine increases quinidine serum concentration by 33% after two days. Amiodarone taken concomitantly with procainamide for less than seven days increases plasma concentrations of procainamide and n-acetyl procainamide by 55% and 33%, respectively.

Loratadine, a non-sedating antihistaminic, is metabolized primarily by CYP3A and its metabolism can be inhibited by amiodarone.

Metabolism of lidocaine can be inhibited by amiodarone. Sinus bradycardia has been reported with oral amiodarone in combination with lidocaine (CYP3A substrate) given for local anesthesia. Seizure, associated with increased lidocaine concentrations, has been reported with concomitant administration of intravenous amiodarone.

Amiodarone can inhibit the metabolism of macrolide/ketolide antibiotics (except for azithromycin) and systemic azole antifungal drugs.

Amiodarone taken concomitantly with digoxin increases the serum digoxin concentration by 70% after one day.

Dextromethorphan is a substrate for both CYP2D6 and CYP3A. Amiodarone inhibits CYP2D6.Chronic (> 2 weeks) oral amiodarone administration impairs metabolism of dextromethorphan can lead to increased serum concentrations.

Cyclophosphamide is a prodrug, metabolized by CYP450 including CYP3A to an active metabolite. The metabolism of cyclophosphamide may be inhibited by amiodarone.

13 NONCLINICAL TOXICOLOGY

13.1 Carcinogenesis, Mutagenesis, Impairment of Fertility

No carcinogenicity studies were conducted with intravenous administration of amiodarone. However, oral amiodarone caused a statistically significant, dose-related increase in the incidence of thyroid tumors (follicular adenoma and carcinoma) in rats. The incidence of thyroid tumors in rats was greater than the incidence in controls even at the lowest dose level tested, i.e., 5 mg/kg/day (much less, on a body surface area basis, than the maximum recommended human maintenance dose of 600 mg/day).

Mutagenicity studies conducted with amiodarone HCl (Ames, micronucleus, and lysogenic induction tests) were negative.

No fertility studies were conducted with intravenous administration of amiodarone. However, in a study in which amiodarone HCl was orally administered to male and female rats, beginning 9 weeks prior to mating, reduced fertility was observed at a dose level of 90 mg/kg/day (approximately 1.4 times the maximum recommended human maintenance dose of 600 mg/day).

14 CLINICAL STUDIES

Apart from studies in patients with VT or VF, described below, there are two other studies of amiodarone showing an antiarrhythmic effect before significant levels of DEA could have accumulated. A placebo-controlled study of intravenous amiodarone (300 mg over 2 hours followed by 1200 mg/day) in post-coronary artery bypass graft patients with supraventricular and 2- to 3-consecutive-beat ventricular arrhythmias showed a reduction in arrhythmias from 12 hours on. A baseline-controlled study using a similar IV regimen in patients with recurrent, refractory VT/VF also showed rapid onset of antiarrhythmic activity; amiodarone therapy reduced episodes of VT by 85% compared to baseline.

The acute effectiveness of intravenous amiodarone in suppressing recurrent VF or hemodynamically unstable VT is supported by two randomized, parallel, dose-response studies of approximately 300 patients each. In these studies, patients with at least two episodes of VF or hemodynamically unstable VT in the preceding 24 hours were randomly assigned to receive doses of approximately 125 or 1000 mg over the first 24 hours, an 8-fold difference. In one study, a middle dose of approximately 500 mg was evaluated. The dose regimen consisted of an initial rapid loading infusion, followed by a slower 6-hour loading infusion, and then an 18-hour maintenance infusion. The maintenance infusion was continued up to hour 48. Additional 10-minute infusions of 150 mg intravenous amiodarone were given for "breakthrough" VT/VF more frequently to the 125 mg dose group, thereby considerably reducing the planned 8-fold differences in total dose to 1.8- and 2.6-fold, respectively, in the two studies.

The prospectively defined primary efficacy end point was the rate of VT/VF episodes per hour. For both studies, the median rate was 0.02 episodes per hour in patients receiving the high dose and 0.07 episodes per hour in patients receiving the low dose, or approximately 0.5 versus 1.7 episodes per day (p=0.07, 2-sided, in both studies). In one study, the time to first episode of VT/VF was significantly prolonged (approximately 10 hours in patients receiving the low dose and 14 hours in patients receiving the high dose). In both studies, significantly fewer supplemental infusions were given to patients in the high-dose group. At the end of double-blind therapy or after 48 hours, all patients were given open access to whatever treatment (including intravenous amiodarone) was deemed necessary. Mortality was not affected in these studies.

16 HOW SUPPLIED/STORAGE AND HANDLING

NEXTERONE (amiodarone HCl) Premixed Injection is supplied as a ready-to-use, sterile, nonpyrogenic, iso-osmotic solution in 100 mL and 200 mL single-dose GALAXY containers packaged in individual cartons as follows:

150 mg/100 mL | NDC 43066 – 150 – 10
360 mg/200 mL | NDC 43066 – 360 – 20

Do not add supplementary medication to NEXTERONE Premixed Injection.

Store at 20° - 25°C (68° - 77°F); excursions permitted to 15° - 30°C (59° - 86°F). See USP Controlled Room Temperature.

Protect from light and excessive heat. Protect from freezing.

Use carton to protect contents from light until used.

Baxter, Galaxy and Nexterone are trademarks of Baxter International Inc. or its subsidiaries

Baxter Healthcare Corporation
Deerfield, IL 60015

07-19-09-163

PACKAGE LABELING - PRINCIPAL DISPLAY PANEL

Container Label

NDC 43066-360-20

Nexterone
(amiodarone HCI)
Premixed Injection

360 mg/200 mL
(1.8 mg/mL)

Rx Only
For Intravenous Use

Galaxy
200mL Single-Dose Container
Discard unused portion

Iso-osmotic solution in Dextrose
Code 2G3450
Sterile, Nonpyrogenic

Each mL contains: 1.8 mg amiodarone HCl, USP; 18 mg Betadex Sulfobutyl Ether Sodium, NF;
0.362 mg citric acid anhydrous, 0.183 mg sodium citrate dihydrate, and 41.4 mg dextrose
anhydrous in water for injection. Sodium hydroxide or hydrochloric acid may have been
added to adjust pH.

CAUTIONS: Check for minute leaks by squeezing bag firmly. If leaks are found, discard bag
as sterility may be impaired. Do not use unless solution is clear.

Do not add supplemental medication. Must not be used in series connections.

Store at 20º to 25º C (68º to 77º F); excursions permitted to 15º to 30º C (59º to 86º F).

See USP Controlled Room Temperature. Protect from freezing. Avoid excessive heat.
USE CARTON TO PROTECT CONTENTS FROM LIGHT UNTIL USE.

Baxter, Galaxy and Nexterone are trademarks of Baxter International Inc. or its subsidiaries.

Baxter Logo
Baxter Healthcare Corporation, Deerfield, IL 60015 USA
Made in the USA

07-34-00-2401

Barcode
3 4306636020 7

Carton Label

Nexterone
(amiodarone HCl)
Premixed Injection
For Intravenous Use

360 mg/200 mL
(1.8 mg/mL)

Nexterone
(amiodarone HCl)
Premixed Injection
For Intravenous Use

360 mg/200 mL
(1.8 mg/mL)

Nexterone
(amiodarone HCl)
Premixed Injection

360 mg/200 mL
(1.8 mg/mL)
For Intravenous Use

UNVARNISHED AREA FOR ON-LINE
PRINTING OF LOT & EXP

Barcode
3 4306636020 7

Iso-osmotic solution in Dextrose
Sterile, Nonpyrogenic

Each mL contains: 1.8 mg amiodarone HCl, USP; 18 mg Betadex Sulfobutyl Ether
Sodium, NF; 0.362 mg citric acid anhydrous, 0.183 mg sodium citrate dihydrate,
and 41.4 mg dextrose anhydrous in water for injection. Sodium hydroxide or
hydrochloric acid may have been added to adjust pH.

Does not contain polysorbate 80 or benzyl alcohol.

Dosage: See prescribing information.

STORAGE: Store at 20º to 25º C (68º to 77º F); excursions permitted to 15º to 30º C
(59º to 86º F). See USP Controlled Room Temperature.
Protect from freezing. Avoid excessive heat.
USE CARTON TO PROTECT CONTENTS FROM LIGHT UNTIL USE.

Baxter, Galaxy and Nexterone are trademarks of Baxter International Inc. or its
subsidiaries.

Baxter Healthcare Corporation
Deerfield, IL 60015 USA

07-01-00-1679

Nexterone
(amiodarone HCl)
Premixed Injection
For Intravenous Use

360 mg/200 mL
(1.8 mg/mL)

Nexterone
(amiodarone HCl)
Premixed Injection
For Intravenous Use

360 mg/200 mL
(1.8 mg/mL)

NDC 43066-360-20
Code 2G3450

Nexterone
(amiodarone HCl)
Premixed Injection

360 mg/200 mL
(1.8 mg/mL)

Rx Only
For Intravenous Use

USE CARTON TO PROTECT
CONTENTS FROM LIGHT UNTIL USE

1 Galaxy Single-Dose Container
Discard unused portion

Baxter Logo
Baxter Healthcare Corporation, Deerfield, IL 60015 USA

Container Label

Nexterone
(amiodarone HCl)
Premixed Injection
For Intravenous Use

150 mg/100 mL
(1.5 mg/mL)

Nexterone
(amiodarone HCl)
Premixed Injection
For Intravenous Use

150 mg/100 mL
(1.5 mg/mL)

Nexterone
(amiodarone HCl)
Premixed Injection
For Intravenous Use

150 mg/100 mL
(1.5 mg/mL)
For Intravenous Use

UNVARNISHED AREA FOR ON-LINE
PRINTING OF LOT & EXP

Barcode
3 4306615010 5

Iso-osmotic solution in Dextrose
Sterile, Nonpyrogenic

Each mL contains: 1.5 mg amiodarone HCl, USP; 15 mg Betadex Sulfobutyl Ether
Sodium, NF; 0.362 mg citric acid anhydrous, 0.183 mg sodium citrate dihydrate,
and 42.1 mg dextrose anhydrous in water for injection. Sodium hydroxide or
hydrochloric acid may have been added to adjust pH.

Does not contain polysorbate 80 or benzyl alcohol.

Dosage: See prescribing information.

STORAGE: Store at 20º to 25º C (68º to 77º F); excursions permitted to 15º to 30º C
(59º to 86º F). See USP Controlled Room Temperature.
Protect from freezing. Avoid excessive heat.
USE CARTON TO PROTECT CONTENTS FROM LIGHT UNTIL USE.

Baxter, Galaxy and Nexterone are trademarks of Baxter International Inc. or its
subsidiaries.

Baxter Healthcare Corporation
Deerfield, IL 60015 USA

07-01-00-1735

Nexterone
(amiodarone HCl)
Premixed Injection
For Intravenous Use

150 mg/100 mL
(1.5 mg/mL)

Nexterone
(amiodarone HCl)
Premixed Injection
For Intravenous Use

150 mg/100 mL
(1.5 mg/mL)

NDC 43066-150-10
Code 2G3451

Nexterone
(amiodarone HCl)
Premixed Injection

150 mg/100 mL
(1.5 mg/mL)

Rx Only
For Intravenous Use

USE CARTON TO PROTECT
CONTENTS FROM LIGHT UNTIL USE

1 Galaxy Single-Dose Container
Discard unused portion

Baxter Logo
Baxter Healthcare Corporation, Deerfield, IL 60015 USA

Carton Label

Nexterone
(amiodarone HCl)
Premixed Injection
For Intravenous Use

150 mg/100 mL
(1.5 mg/mL)

Nexterone
(amiodarone HCl)
Premixed Injection
For Intravenous Use

150 mg/100 mL
(1.5 mg/mL)

Nexterone
(amiodarone HCl)
Premixed Injection

150 mg/100 mL
(1.5 mg/mL)
For Intravenous Use

UNVARNISHED AREA FOR ON-LINE
PRINTING OF LOT & EXP

Lot ABXXXXXX
EXP YYY-MM-DD

*FOR BAR CODE
POSITION ONLY

(01) 00000000000000
(10)XX0000000
(21) 000000000000
(17)0000000000

Barcode
3 4306615010 5

Iso-osmotic solution in Dextrose
Sterile, Nonpyrogenic

Each mL contains: 1.5 mg amiodarone HCl, USP; 15 mg Betadex Sulfobutyl Ether
Sodium, NF; 0.362 mg citric acid anhydrous, 0.183 mg sodium citrate dihydrate,
and 42.1 mg dextrose anhydrous in water for injection. Sodium hydroxide or
hydrochloric acid may have been added to adjust pH.

Does not contain polysorbate 80 or benzyl alcohol.

DOSAGE: See prescribing information.

STORAGE: Store at 20º to 25º C (68º to 77º F); excursions permitted to 15º to 30º C
(59º to 86º F). See USP Controlled Room Temperature.
Protect from freezing. Avoid excessive heat.
USE CARTON TO PROTECT CONTENTS FROM LIGHT UNTIL USE.

Baxter, Galaxy and Nexterone are trademarks of Baxter International Inc. or its
subsidiaries.

Baxter Healthcare Corporation
Deerfield, IL 60015 USA

07-01-00-1735

Nexterone
(amiodarone HCl)
Premixed Injection
For Intravenous Use

150 mg/100 mL
(1.5 mg/mL)

Nexterone
(amiodarone HCl)
Premixed Injection
For Intravenous Use

150 mg/100 mL
(1.5 mg/mL)

NDC 43066-150-10
Code 2G3451

Nexterone
(amiodarone HCl)
Premixed Injection

150 mg/100 mL
(1.5 mg/mL)

Rx Only
For Intravenous Use

USE CARTON TO PROTECT
CONTENTS FROM LIGHT UNTIL USE

1 GALAXY Single-Dose Container
Discard unused portion

Baxter Logo
Baxter Healthcare Corporation, Deerfield, IL 60015 USA